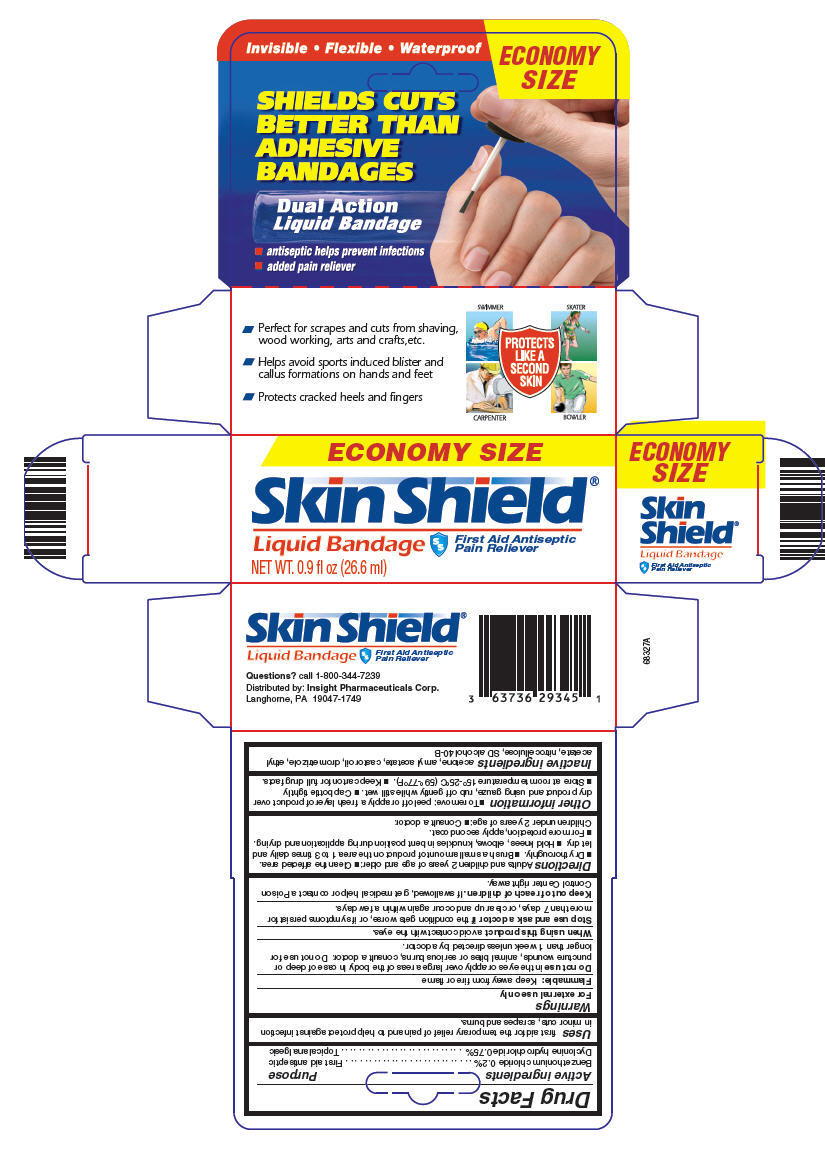 DRUG LABEL: Skin Shield
NDC: 63736-293 | Form: LIQUID
Manufacturer: Insight Pharmaceuticals
Category: otc | Type: HUMAN OTC DRUG LABEL
Date: 20100622

ACTIVE INGREDIENTS: Benzethonium Chloride 0.0532 mL/27 mL; Dyclonine Hydrochloride 0.0997 mL/27 mL
INACTIVE INGREDIENTS: Acetone; Amyl Acetate; Castor Oil; Drometrizole; Ethyl Acetate

Skin Shield®
Liquid Bandage

Drug Facts

ACTIVE INGREDIENT

Active ingredients | Purpose
Benzethonium chloride 0.2% | First aid antiseptic
Dyclonine hydrochloride 0.75% | Topical analgesic

Uses

first aid for the temporary relief of pain and to help protect against infection in minor cuts, scrapes and burns.

Warnings

For external use only

Flammable: Keep away from fire or flame

Do not use in the eyes or apply over large areas of the body. In case of deep or puncture wounds, animal bites or serious burns, consult a doctor. Do not use for longer than 1 week unless directed by a doctor.

When using this product avoid contact with the eyes.

Stop use and ask a doctor if the condition gets worse, or if symptoms persist for more than 7 days, or clear up and occur again within a few days.

Keep out of reach of children. If swallowed, get medical help or contact a Poison Control Center right away.

Directions

Adults and children 2 years of age and older:

- Clean the affected area.
- Dry thoroughly.
- Brush a small amount of product on the area 1 to 3 times daily and let dry.
- Hold knees, elbows, knuckles in bent position during application and drying.
- For more protection, apply second coat.

Children under 2 years of age:

- Consult a doctor.

Other information

- To remove: peel off or apply a fresh layer of product over dry product and using gauze, rub off gently while still wet.
- Cap bottle tightly
- Store at room temperature 15°-25°C (59°-77°F).
- Keep carton for full drug facts.

Inactive ingredients

acetone, amyl acetate, castor oil, drometrizole, ethyl acetate, nitrocellulose, SD alcohol 40-B

Questions?

call 1-800-344-7239

Distributed by: Insight Pharmaceuticals Corp.
Langhorne, PA 19047-1749

PRINCIPAL DISPLAY PANEL - 26.6 ml Bottle Carton

ECONOMY SIZE

Skin Shield®
Liquid Bandage
First Aid Antiseptic
Pain Reliever

NET WT. 0.9 fl oz (26.6 ml)